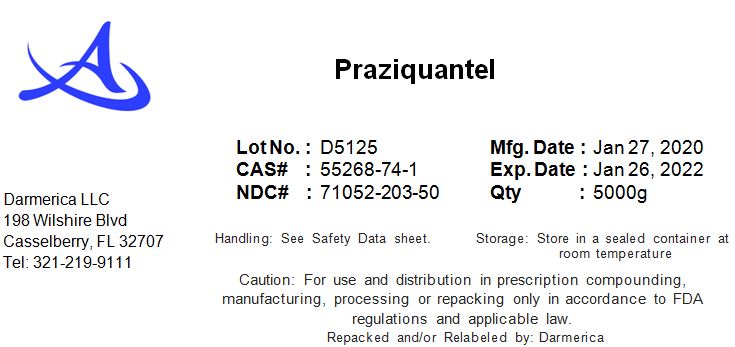 DRUG LABEL: Praziquantel
NDC: 71052-203 | Form: POWDER
Manufacturer: DARMERICA, LLC
Category: other | Type: BULK INGREDIENT
Date: 20200310

ACTIVE INGREDIENTS: PRAZIQUANTEL 500 g/500 g

Praziquantel